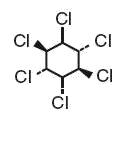 DRUG LABEL: Unknown
Manufacturer: Olta Pharmaceuticals Corporation
Category: prescription | Type: HUMAN PRESCRIPTION DRUG LABEL
Date: 20090317

LINDANE LOTION USP, 1%

Rx only

WARNINGS

Lindane Lotion should only be used in patients who cannot tolerate or have failed first-line treatment with safer medications for the treatment of scabies. (See INDICATIONS AND USAGE.)

Neurologic Toxicity

Seizures and deaths have been reported following Lindane Lotion use with repeat or prolonged application, but also in rare cases following a single application used according to directions. Lindane Lotion should be used with caution for infants, children, the elderly, and individuals with other skin conditions (e.g., atopic dermatitis, psoriasis) and in those who weigh < 110 lbs (50 kg) as they may be at risk of serious neurotoxicity.

Contraindications

Lindane Lotion is contraindicated in premature infants and individuals with known uncontrolled seizure disorders.

Proper Use

Instruct patients on the proper use of Lindane Lotion, the amount to apply, how long to leave it on, and avoiding retreatment. Inform patients that itching occurs after the successful killing of scabies and is not necessarily an indication for retreatment with Lindane Lotion. (See DOSAGE AND ADMINISTRATION.)

DESCRIPTION

Lindane Lotion USP, 1%, is an ectoparasiticide and ovicide. In addition to the active ingredient, lindane, it contains 2-amino-2-methyl-1-propanol, butylparaben, carrageenan, cetyl alcohol, glyceryl monostearate, methylparaben, perfume compound, purified water, stearic acid and triethanolamine to form a lotion. The pH range is between 6.5 and 8.5. Lindane is the gamma isomer of 1,2,3,4,5,6-hexachlorocyclohexane having the following structural formula:

C6H6Cl6 M.W. 290.83

CLINICAL PHARMACOLOGY

Lindane Lotion USP, 1%, is an ectoparasiticide and ovicide effective against Sarcoptes scabiei (scabies). Lindane exerts its parasiticidal action by being directly absorbed into the parasites and their ova. Feldmann and Maibach^1 reported approximately 10% systemic absorption of a lindane acetone solution when applied to the forearm of human subjects and left in place for 24 hours. This vehicle was different from the approved product and the percutaneous penetration of lindane is dependent on the vehicle. Therefore, the clinical significance of these observations is unknown. Dale, et al^2 reported a blood level of 290 ng/mL associated with convulsions following the accidental ingestion of a lindane-containing product. Ginsburg ^3 found the greatest peak blood level of 64 ng/mL, 6 hours after total body application of Lindane Lotion in 1 of 8 non-scabietic pediatric patients. The half-life in blood was determined to be approximately 18 hours.

Data available in the literature suggest that lindane has a rapid distribution phase followed by a longer β-elimination phase.^(1, 2, 3)

INDICATIONS AND USAGE

Lindane Lotion is indicated for the treatment of scabies (infestations of Sarcoptes scabei) only in patients who:

1. cannot tolerate other approved therapies, or
2. have failed treatment with other approved therapies.

Lindane Lotion should be used in the context of an overall scabies management program that includes:

- Microscopic evaluation of skin scrapings to confirm the diagnosis.
- Evaluation and treatment of sexual contacts simultaneously. Sexual contacts should be prescribed Lindane Lotion only if they either have failed to respond to adequate doses of other approved therapies or are intolerant of other approved therapies.
- Washing of all recently worn clothing, underwear, pajamas, used sheets, pillowcases, and towels in very hot water or dry-cleaned.

Caregivers applying this product to patients should wear gloves less permeable to Lindane, such as nitrile, latex with neoprene, or sheer vinyl, and thoroughly clean hands after application. Natural latex gloves should be avoided because they are more permeable to Lindane.

Lindane Lotion does not prevent infestation or reinfestation and should not be used to ward off a possible infestation.

CONTRAINDICATIONS

Lindane Lotion is contraindicated for premature infants because their skin may be more permeable than that of full term infants and their liver enzymes may not be sufficiently developed to metabolize Lindane.

Lindane Lotion is also contraindicated for patients with crusted (Norwegian) scabies and other skin conditions (e.g., atopic dermatitis, psoriasis) that may increase systemic absorption of the drug.

Lindane Lotion is contraindicated for patients with known uncontrolled seizure disorders and for individuals with a known sensitivity to the product or any of its components.

WARNINGS

(See boxed WARNINGS.)

Seizures and deaths have been reported following Lindane Lotion's use with repeat or prolonged application, but also in rare cases following a single application reportedly used according to directions. It is not known how soon after application of a single dose of Lindane Lotion that a second dose of Lindane Lotion can be safely applied.

There have been cases of adverse events reported for Lindane Lotion and Lindane Shampoo in which a serious outcome (hospitalization, disability or death) has occurred.^4 In approximately 20% of the total reported cases, Lindane Lotion and Shampoo were reported to have been used according to the labeled directions. Of these cases, thirteen deaths were reported, many cases which were remote from the time of actual Lindane use. Lindane toxicity, verified by autopsy was the cause of one infant's death, was the cause of death reported for an adult who ingested it orally in a successful suicide. The direct causes of death for the other cases were attributed to reasons other than Lindane. Most of these adverse events occurred with Lindane Lotion.

Infants, children, the elderly, and individuals with other skin conditions and those who weigh < 110 lbs (50 kg) may be at greater risk of serious neurotoxicity. (See Pediatric Use and Geriatric Use.) Animal studies have shown increased susceptibility to neurologic adverse events in younger animals. Children have a larger body surface area to volume ratio that may result in a proportionately larger systemic exposure.

Careful consideration should be given before prescribing Lindane Lotion to patients with conditions that may increase the risk of seizure, such as HIV infection, history of head trauma or a prior seizure, CNS tumor, the presence of severe hepatic cirrhosis, excessive use of alcohol, abrupt withdrawal from alcohol or sedatives, as well as concomitant use of medications known to lower seizure threshold. (See PRECAUTIONS: Drug Interactions.)

Patients should be instructed on proper use of Lindane Lotion, especially the amount to apply, how long to leave the lotion on, and the need to avoid retreatment. Patients should be informed that itching may occur, and even worsen, after the successful killing of scabies. Repeat treatment is usually not necessary.

A Lindane Lotion Medication Guide must be given to the patient each time Lindane Lotion is dispensed, as required by law.

PRECAUTIONS

General

Care should be taken to avoid contact with the eyes. If such contact occurs, eyes should be immediately flushed with water. If irritation or sensitization occurs, the patient should be advised to consult a physician.

Information for Patients (and Caregivers)

- This product can be poisonous if misused.
- Other important information is found in the Medication Guide, which by law, must be dispensed with Lindane Lotion.
- If someone other than the patient will be applying Lindane Lotion to the patient, they should wear less permeable gloves such as nitrile, latex with neoprene, or sheer vinyl, and thoroughly clean their hands after application. Natural latex gloves should be avoided because they are more permeable to lindane.
- If the person applying Lindane Lotion could be pregnant, contact with Lindane Lotion should be avoided as much as possible.
- If the patient could be pregnant, other treatments may be preferable.
- Lindane Lotion should be used for scabies only.
- The skin should be clean and without any other lotion, cream, or oil on it. Oils can make the Lindane Lotion go through the skin faster and possibly increase the risk of neurotoxicity (e.g., seizures).
- Wait at least 1 hour after bathing or showering before putting Lindane Lotion on the skin. Wet or warm skin can make the Lindane Lotion go through skin faster.
- Information for Use:
  - Shake Lindane Lotion well.
  - Put Lindane Lotion under fingernails after trimming the fingernails short, because scabies are very likely to remain there. A toothbrush can be used to apply the Lindane Lotion under the fingernails. Immediately after use, the toothbrush should be wrapped in paper and thrown away. Use of the same brush in the mouth could lead to poisoning.
  - Use only a single application, applied as a very thin layer over all skin from the neck down.
  - Close the bottle with the leftover Lindane Lotion and immediately throw it away in a trash can out of the reach of children.
  - Do not use any covering over the applied Lindane Lotion that does not breathe, like diapers with plastic lining, plastic clothes, tight clothes, or blankets.
  - Wash the Lindane Lotion completely off after 8 to 12 hours. Never leave Lindane Lotion on the skin for more than 12 hours. Warm, but not hot water can be used. Lindane Lotion will not kill any more scabies after 8 to 12 hours, but may cause serious health problems.
  - Keep Lindane Lotion away from mouth and eyes. If contact with eyes occurs, immediately flush eyes with water. Do not use if you have open wounds, cuts or sores that are present, unless specifically directed by the prescribing physician.
  - All recently worn clothing, underwear, pajamas, used sheets, pillowcases, and towels should be washed in very hot water or dry-cleaned.
  - The patient may still itch after using Lindane Lotion. This does not mean the medicine did not work. Even after all the scabies (bugs) are dead, they can still make the skin itch for a few weeks. Lindane Lotion sometimes makes this itch even worse. Other treatments can be used to soothe the itch. Do not use more Lindane Lotion.
  - The patient should contact the physician with any questions or concerns about his or her condition or use of the Lindane Lotion.

Drug Interactions

Oils may enhance absorption of Lindane, therefore, patients or caregivers applying Lindane Lotion should be warned about simultaneous use of creams, ointments, or oils. In addition, there are many drugs that may lower the seizure threshold, and Lindane Lotion should be prescribed with caution in patients taking these medications. Drugs that may lower the seizure threshold include, but are not limited to the following:

- Antipsychotics
- Antidepressants
- Theophylline
- Cyclosporine, mycophenolate mofetil, tacrolimus capsules
- Penicillins, imipenem, quinolone antibiotics
- Chloroquine sulfate, pyrimethamine
- Isoniazid
- Meperidine
- Radiographic contrast agents
- Centrally active anticholinesterases
- Methocarbamol

Carcinogenesis, Mutagenesis, and Fertility

Although no studies have been conducted with Lindane Lotion, numerous long-term feeding studies have been conducted in mice and rats to evaluate the carcinogenic potential of the technical grade of hexachlorocyclohexane as well as the alpha, beta, gamma (lindane) and delta isomers. Both oral and topical applications have been evaluated. Increased incidences of neoplasms were not clearly related to administration of lindane. The results of mutagenicity tests in bacteria do not indicate that lindane is mutagenic. Lindane did not cause sister chromatid exchange in an in vivo assay. The number of spermatids in the testes of rats 2 weeks after oral administration of a single dose of 30 mg/kg body weight (12 times the estimated human exposure for scabies on a body surface area comparison and assuming 50% rat oral bioavailability and 10% human bioavailability) was significantly reduced compared to the control rats.

Pregnancy

Pregnancy Category C

All pregnancies have a risk of birth defect, loss, or other adverse event regardless of drug exposure. Predictions of fetal risk from drug exposure rely heavily on animal data. However, animal studies may fail to predict effects in humans or may overstate such risks. Even if human data are available, the data may not be sufficient to determine whether there is an increased risk to the fetus, and individual reports of adverse outcomes in pregnancy in association with a drug may not reflect a causal relationship.

Lindane Lotion should be given to pregnant women only if clearly needed. There are no adequate and well-controlled studies of Lindane Lotion in pregnant women. There are no known maternal or fetal health risks if the scabies is not treated. Lindane is lipophilic and may accumulate in the placenta. There has been a single case report of a stillborn infant following multiple maternal exposures to lindane during pregnancy. The relationship of the maternal exposures to the fetal outcome is unknown.

Animal data suggest that lindane exposure of the fetus may increase the likelihood of neurologic developmental abnormalities (see below), based on findings at systemic exposures close to that expected in humans when Lindane Lotion is used to treat scabies. The immature central nervous system (as in the fetus) may have increased susceptibility to the effects of the drug.

Data

When rats received lindane in the diet from day 6 of gestation through day 10 of lactation, reduced pup survival, decreased pup weight and decreased weight gains during lactation, increased motor activity and decreased motor activity habituation were seen in pups at 5.6 mg/kg (2 times the estimated human exposure) but not at 1.2 mg/kg. An increased number of stillborn pups was seen at 8 mg/kg, and increased pup mortality was seen at 5.6 mg/kg. No gross abnormalities were seen in this study or in a study in which rabbits received up to 20 mg/kg lindane by gavage on gestation day 6–18 (up to 10 times the human exposure on a body surface area comparison and assuming 50% rabbit oral bioavailability and 10% human bioavailability).

Nursing Mothers

Lindane is lipophilic and is present in human breast milk, but exact quantities are not known. There may be a risk of toxicity if lindane is ingested from breast milk, or from skin absorption from mother to baby in the course of breast-feeding when Lindane Lotion is applied topically to the chest area. Nursing mothers who require treatment with Lindane Lotion should be advised of the potential risks and be counseled to avoid large areas of skin-to-skin contact with the infant while Lindane Lotion is applied, as well as to interrupt breast-feeding, with expression and discarding of milk, for at least 24 hours following use.

Pediatric Use

Animal data demonstrated increased risk of adverse events in the young across species. Pediatric patients have a higher surface to volume ratio and may be at risk of greater systemic exposure when Lindane Lotion is applied to the body. Infants and children may be at an even higher risk due to immaturity of organ systems such as skin and liver. Lindane Lotion should be used with extreme caution in patients who weigh less than approximately 110 lbs (50 kg) and especially in infants. Lindane Lotion is indicated only for the treatment of scabies; patients with lice should use Lindane Shampoo according to the labeled instructions.

Geriatric Use

There have been no studies of Lindane Lotion in the elderly. There are four postmarketing reports of deaths in elderly patients who were treated for scabies with Lindane Lotion. Two patients died within 24 hours of Lindane Lotion application, and the third patient died 41 days after application of Lindane Lotion, having suffered a seizure on the day of death. A fourth patient died of an unreported cause of death on the same day that Lindane Lotion treatment for scabies was administered.

ADVERSE REACTIONS

Lindane Lotion has been reported to cause central nervous system stimulation ranging from dizziness to seizures. Although seizures were almost always associated with ingestion or misuse of the product (to include repeat treatment), seizures and deaths have been reported when Lindane Lotion was used according to directions. Irritant dermatitis from contact with this product has also been reported. (See WARNINGS, PRECAUTIONS, and DOSAGE AND ADMINISTRATION.)

Postmarketing Experience

The following adverse reactions reflect additional postmarketing experience of Lindane Lotion. These events include alopecia, dermatitis, headache, pain, paresthesia, pruritus and urticaria. The relationship of some of these events to Lindane therapy is unknown.

OVERDOSAGE

Contact the closest Poison Control Center in the event of suspected overdosage with Lindane Lotion.

If accidental ingestion occurs, prompt gastric lavage should be instituted. However, since oils enhance absorption, saline cathartics for intestinal evacuation should be given rather than oil laxatives. If central nervous system (CNS) manifestations occur, they may be antagonized by the administration of pentobarbital, phenobarbital, or diazepam.

DOSAGE AND ADMINISTRATION

Apply a thin layer of Lindane Lotion over all skin from the neck down. One ounce is sufficient for an average adult. Do not prescribe more than 2 ounces for larger adults. Apply only once. Wash off in 8 to 12 hours. Do not retreat. (See boxed WARNINGS.)

Patients should be provided specific information on use of product. (See PRECAUTIONS: Information for Patients and the Medication Guide.) Patients should be instructed on proper use of Lindane Lotion, especially the amount to apply, how long to leave on and the need to avoid retreatment. Patients should be informed that itching occurs after the successful killing of scabies (lice) and continued itching is not necessarily an indication for retreatment with Lindane Lotion.

A Lindane Lotion Medication Guide must be given to the patient each time Lindane Lotion is dispensed, as required by law. The Lindane Lotion Medication Guide is an important part of the risk management program for the patient.

HOW SUPPLIED

Lindane Lotion USP, 1% is supplied in 1 fl oz (30 mL) (NDC#: 45068-101-01) and 2 fl oz (60 mL) (NDC#: 45068-101-02) bottles.

SHAKE WELL BEFORE USING

STORAGE AND HANDLING

Store at 20° - 25°C (68° - 77°F) [See USP Controlled Room Temperature].

REFERENCES

1. Feldmann, R.J. and Maibach, H.I., Toxicol. Applied. Pharmacol., 28:126, 1974.
2. Dale, W.E., Curly, A. and Cueto, C. Life Sci 5:47, 1966.
3. Ginsburg, C.M., et al., J. Pediatr. 91:6, 998–1000, 1977.
4. FDA AERS database search, January 2003

Manufactured by:
AL&S, LLC
De Kalb, MS 39328.

Marketed by:
Olta Pharmaceuticals Corporation.
Warminster, PA 18974.

IOP10102-00
Issued: 02-17-2009

PHARMACIST—PATIENT MEDICATION GUIDE PROVIDED BELOW

MEDICATION GUIDE

Lindane (LIHN-dane) Lotion USP, 1%

You must read and follow all instructions before using Lindane Lotion. Read the information you get every time you or a family member get Lindane Lotion. There may be new information. This Medication Guide does not take the place of talking with your doctor about your medical condition or treatment. If you have any questions about Lindane Lotion, ask your doctor or pharmacist.

What is the most important information I should know about Lindane Lotion?

Lindane Lotion is a poison if you do not use it the right way. Lindane Lotion goes through your skin and may affect your brain and nerves. Lindane Lotion can cause seizures, also called convulsions, "fits" or epilepsy.

- Seizures and death can happen in people who use Lindane Lotion too much or too often.
- Seizures can happen in some people even if they use Lindane Lotion exactly as directed.

If you or a family member has a seizure while using Lindane Lotion, get emergency help right away.

- Do not use Lindane Lotion unless:
  - You have scabies and were treated with another medicine that did not work for you, or
  - You cannot use other safer medicines to treat your scabies.
- Do not use Lindane Lotion more than 1 time to treat an attack of scabies. Do not use Lindane Lotion to treat a second attack of scabies that comes soon after the first episode. Using it more than 1 time can cause seizures and death. No one knows a safe time to reuse Lindane Lotion. Even if you still itch after using Lindane Lotion, do not use more or use it again. Scabies (bugs) can make your skin itch for a few weeks even after all of the bugs are dead.
- Do not use more Lindane Lotion than your doctor tells you.
- Do not keep Lindane Lotion on your skin for more than 8 to 12 hours.
- Do not put Lindane Lotion in your mouth because it is a poison if taken by mouth. If you get Lindane Lotion in your mouth or swallow Lindane Lotion, call your area Poison Control Center right away and get emergency help.

What is Lindane Lotion?

Lindane Lotion is a medicine that is used to treat scabies. It kills scabies and their eggs. Scabies are very small bugs that crawl under your skin, lay eggs, and cause severe itching. Lindane Lotion goes through your skin and kills the scabies and their eggs. Lindane Lotion is used only after safer medicines have not made your scabies go away. The only time Lindane Lotion is used first is when someone cannot use safer medicines, which may include permethrin and crotamiton.

Lindane Lotion is mainly for adults and children who weigh at least 110 pounds. If you weigh less than 110 pounds, use Lindane Lotion only if your doctor thinks it is really needed. People who weigh less than 110 pounds and the elderly have higher chances for side effects because more lindane may go through their skin.

Who should not use Lindane Lotion?

Do not use Lindane Lotion:

- if you do not have scabies. Lindane Lotion does not stop you from getting scabies. Lindane Lotion only kills the scabies you already have.
- if you have or have ever had seizures, also called convulsions, "fits" or epilepsy, especially if they have been hard to control.
- if you used Lindane Lotion in the past few months. You should see your doctor if you think you need another treatment.
- unless it is the only medicine you can use for scabies.
- if you had a bad reaction to Lindane Lotion before. Do not use Lindane Lotion again.
- if you have open sores or crusted (scabby) sores on your skin, or lots of broken skin.
- if you have head or body lice. These need a different medicine that you use in a different way.
- if you are allergic to Lindane Lotion or any of its ingredients. The active ingredient is lindane. See the end of this Medication Guide for a list of all the ingredients in Lindane Lotion.
- if you need to treat a premature or young baby. More lindane can go through the skin of babies and go to their brains where it can harm them.
- while you are breast-feeding. Lindane Lotion can get in your milk and be fed to your baby. Lindane Lotion on your skin can also go to your baby. Your baby may get sick. Ask your doctor for a safer medicine. If you use Lindane Lotion, pump your breast milk and throw away the milk for at least 24 hours after using the medicine. During this time, feed your baby formula or breast milk you stored from before you used Lindane Lotion.

Tell your doctor if you:

- used Lindane Lotion in the past few months.
- ever had a seizure or problem that could increase your chances of getting a seizure (like a head injury, tumor in your brain or spinal cord, cirrhosis of the liver, or heavy alcohol drinking.)
- have HIV or AIDS. Lindane Lotion may cause seizures even if you never had them before.
- are pregnant. Lindane Lotion can reach your baby and may harm it. Ask your doctor for a safer medicine. Use Lindane Lotion only if needed.
- have a sexual partner. Your partner should get checked and treated for scabies so they don't give them back to you. Don't share your Lindane Lotion with your partner.

Tell your doctor about all the medicines you take, including prescription and non-prescription medicines, vitamins, and herbal supplements. Some medicines may increase your chances of having a seizure if you take them while using Lindane Lotion. Especially, tell your doctor if you take medicines called sedatives (drugs to help you sleep).

How do I use Lindane Lotion?

Before you put it on:

- Make sure you know how to use it exactly as your doctor prescribes.
- If you are putting Lindane Lotion on another person, wear special gloves made of nitrile, latex with neoprene, or sheer vinyl. Do not use natural latex gloves because more lindane can go through that kind of glove. Wash your hands well when you are done.
- Make sure your skin is clean and does not have any other lotion, cream, or oil on it. Oils can make Lindane Lotion go through your skin faster and may increase the risk of seizures.
- Wait for at least 1 hour after bathing or showering before you put Lindane Lotion on your skin. Wet or warm skin can make the Lindane Lotion go through your skin faster and may increase the risk of seizures.

When you put it on:

- Shake the bottle of Lindane Lotion well.
- Put Lindane Lotion under your fingernails, because the scabies really like to stay there. Trim your fingernails short. Use a toothbrush to get the Lindane Lotion under your fingernails. Wrap this toothbrush in paper and throw this toothbrush away. Do not use it in your mouth.
- Put a very thin layer of the Lindane Lotion on your skin from the neck down. You may have some Lindane Lotion left in the bottle.
- Do not cover over the Lindane Lotion on your skin with anything that does not breathe, like diapers with a plastic lining, plastic clothes, tight clothes, or blankets.
- Close the bottle with the leftover Lindane Lotion and throw it away in a trash can out of the reach of children.

When you are supposed to wash it off:

- Wash the Lindane Lotion off your skin after 8 to 12 hours. You must wash the Lindane Lotion off your body completely. Use warm, but not hot water. Lindane Lotion will not kill any more scabies after 8 to 12 hours. After 8 to 12 hours, Lindane Lotion can cause serious health problems, such as seizures and death.

After you wash off the Lindane Lotion:

- All recently worn clothing, underwear, pajamas, used sheets, pillowcases, and towels should be washed in very hot water or dry-cleaned.
- Do not use Lindane Lotion again. If you think you need to use it again, you must check with your doctor to find out when it is most safe.

You may still itch after you use Lindane Lotion. This does not mean you need more Lindane Lotion. Even after all the scabie bugs are dead, they can still make your skin itch for a few weeks. Lindane Lotion sometimes makes this itch even worse. Talk to your doctor about things you can do to soothe the itch.

What should I avoid while using Lindane Lotion?

- Do not get Lindane Lotion in your eyes. If you do, rinse your eyes with water right away. Get medical help if your eyes keep hurting.
- Do not let your skin touch other people's skin while you have Lindane Lotion on. Make sure your skin does not touch your baby or small child.
- If you are pregnant, do not use Lindane Lotion, or apply Lindane Lotion to others unless it is needed and you have talked to your doctor about using it. See the special glove advice below if you have to put Lindane Lotion on others.
- Do not use oils on your skin or hair just before or after using Lindane Lotion. Oils include skin lotions and moisturizers, and oil-based hair products and conditioners.
- Do not get Lindane Lotion on your hands if you are putting it on someone else.Wear special gloves made of nitrile, latex with neoprene, or sheer vinyl. Do not use natural latex gloves. Wash your hands well when you are done.

What are the possible side effects of Lindane Lotion?

Lindane Lotion may cause serious side effects such as seizures (convulsions, fits) or death (See the section, "What is the most important information I should know about Lindane Lotion?"). Lindane Lotion can also make you feel sleepy, dizzy, or can cause body shaking that you cannot control.

The most common side effects of Lindane Lotion are:

- Itching skin
- Burning skin
- Dry skin
- A skin rash

These are not all of the possible side effects of Lindane Lotion. For more information, ask your doctor or pharmacist.

General Information about Lindane Lotion:

Medicines are sometimes prescribed for purposes other than those listed in Medication Guides. Do not use Lindane Lotion for any condition for which it was not prescribed. Do not give Lindane Lotion to other people, even if they have the same symptoms that you have. It may harm them. Keep Lindane Lotion and all medicines out of the reach of children.

This Medication Guide summarizes the most important information about Lindane Lotion. If you want more information, talk with your doctor. You can ask your doctor or pharmacist for information about Lindane Lotion that is written for health professionals.

"Call your doctor for medical advice about side effects. You may report side effects to FDA at 1800-FDA-1088"

What are the ingredients in Lindane Lotion?

Active Ingredient: Lindane.

Inactive Ingredients: 2-amino-2-methyl-1-propanol, butylparaben, carrageenan, cetyl alcohol, glyceryl monostearate, methylparaben, perfume compound, purified water, stearic acid and triethanolamine.

This Medication Guide has been approved by the U.S. Food and Drug Administration.

This medication is available only by a prescription from your doctor.

Manufactured by:
AL&S, LLC
De Kalb, MS 39328.

Marketed by:
Olta Pharmaceuticals Corporation.
Warminster, PA 18974.

GOP10102-00
Issued: 02-17-2009